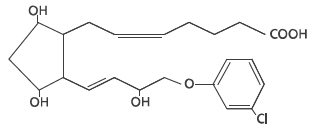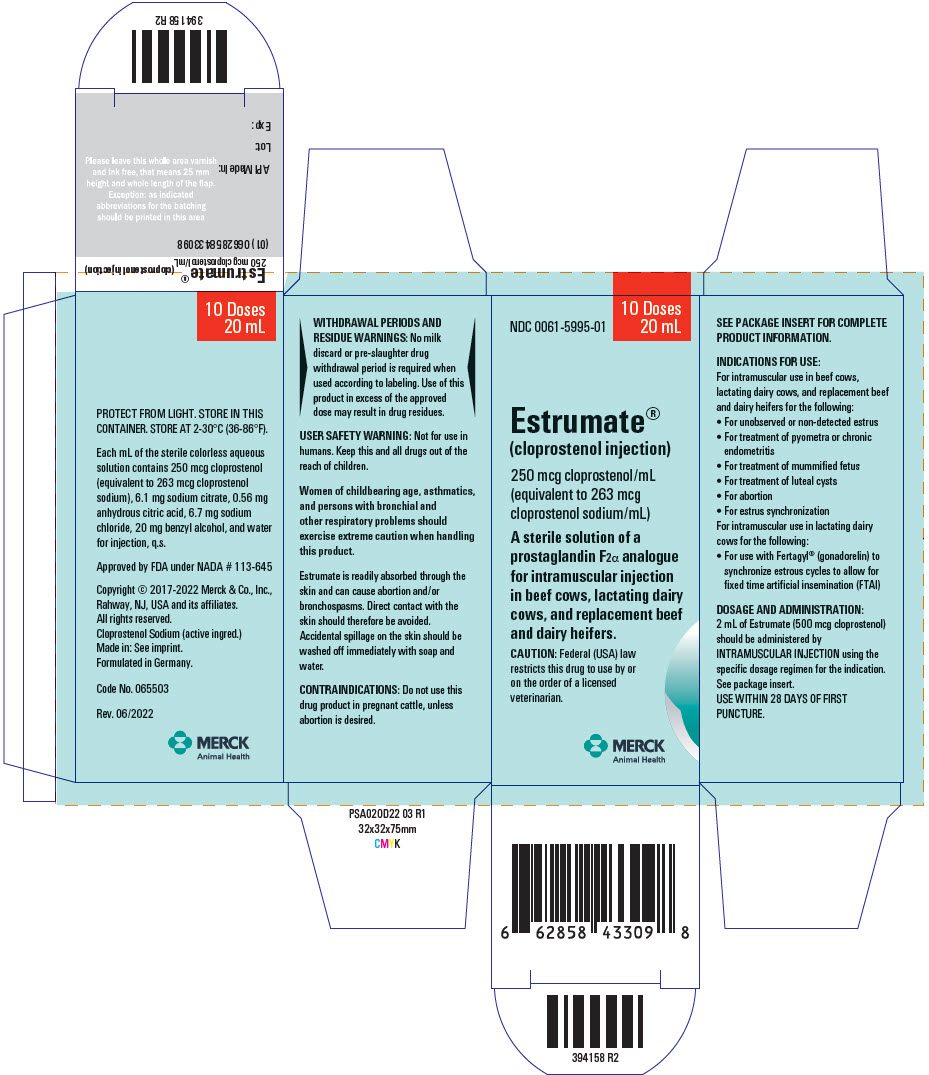 DRUG LABEL: Estrumate
NDC: 0061-5995 | Form: INJECTION
Manufacturer: Merck Sharp & Dohme Corp.
Category: animal | Type: PRESCRIPTION ANIMAL DRUG LABEL
Date: 20241101

ACTIVE INGREDIENTS: CLOPROSTENOL SODIUM 263 ug/1 mL

Estrumate®
(cloprostenol injection)

250 mcg cloprostenol/mL (equivalent to 263 mcg cloprostenol sodium/mL)

A sterile solution of a prostaglandin F2α analogue for intramuscular injection in beef cows, lactating dairy cows, and replacement beef and dairy heifers

Caution: Federal (USA) law restricts this drug to use by or on the order of a licensed veterinarian.

DESCRIPTION:

Estrumate® (cloprostenol injection) is a synthetic prostaglandin analogue structurally related to prostaglandin F2 α (PGF2 α). Each mL of the sterile colorless aqueous solution contains 250 mcg cloprostenol (equivalent to 263 mcg cloprostenol sodium), 6.1 mg sodium citrate, 0.56 mg anhydrous citric acid, 6.7 mg sodium chloride, 20 mg benzyl alcohol, and water for injection, q.s.

INDICATIONS FOR USE:

1. For unobserved or non-detected estrus in beef cows, lactating dairy cows, and replacement beef and dairy heifers
2. For treatment of pyometra or chronic endometritis in beef cows, lactating dairy cows, and replacement beef and dairy heifers
3. For treatment of mummified fetus in beef cows, lactating dairy cows, and replacement beef and dairy heifers
4. For treatment of luteal cysts in beef cows, lactating dairy cows, and replacement beef and dairy heifers
5. For abortion of beef cows, lactating dairy cows, and replacement beef and dairy heifers
6. For estrus synchronization in beef cows, lactating dairy cows, and replacement beef and dairy heifers
7. For use with Fertagyl® (gonadorelin) to synchronize estrous cycles to allow for fixed time artificial insemination (FTAI) in lactating dairy cows.

Estrumate causes functional and morphological regression of the corpus luteum (luteolysis) in cattle. In normal, non-pregnant cycling animals, this effect on the life span of the corpus luteum usually results in estrus 2 to 5 days after treatment. In animals with prolonged luteal function (pyometra, mummified fetus, and luteal cysts), the induced luteolysis usually results in resolution of the condition and return to cyclicity. Pregnant animals may abort depending on the stage of gestation.

DOSAGE AND ADMINISTRATION:

Two mL of Estrumate (500 mcg cloprostenol) should be administered by INTRAMUSCULAR INJECTION using the specific dosage regimen for the indication.

20 mL bottle size: Use within 28 days of first puncture.

100 mL bottle size: Use within 28 days of first puncture and puncture a maximum of 12 times. Use only with automatic injection equipment or repeater syringe. Discard bottle after one stopper puncture with draw-off spike.

1. For unobserved or non-detected estrus in beef cows, lactating dairy cows, and replacement beef and dairy heifers
  Cows and heifers which are not detected in estrus, although ovarian cyclicity continues, can be treated with Estrumate if a mature corpus luteum is present. Estrus is expected to occur 2 to 5 days following injection, at which time animals may be inseminated. Treated cattle should be inseminated at the usual time following detection of estrus. If estrous detection is not desirable or possible, treated animals may be inseminated twice at about 72 and 96 hours post-injection.
2. For treatment of pyometra or chronic endometritis in beef cows, lactating dairy cows, and replacement beef and dairy heifers
  Damage to the reproductive tract at calving or postpartum retention of the placenta often leads to infection and inflammation of the uterus (endometritis). Under certain circumstances, this may progress into chronic endometritis with the uterus becoming distended with purulent matter. This condition, commonly referred to as pyometra, is characterized by a lack of cyclical estrous behavior and the presence of a persistent corpus luteum. Induction of luteolysis with Estrumate usually results in evacuation of the uterus and a return to normal cyclical activity within 14 days after treatment. After 14 days post-treatment, recovery rate of treated animals will not be different than that of untreated cattle.
3. For treatment of mummified fetus in beef cows, lactating dairy cows, and replacement beef and dairy heifers
  Death of the conceptus during gestation may be followed by its degeneration and dehydration. Induction of luteolysis with Estrumate usually results in expulsion of the mummified fetus from the uterus. (Manual assistance may be necessary to remove the fetus from the vagina). Normal cyclical activity usually follows.
4. For treatment of luteal cysts in beef cows, lactating dairy cows, and replacement beef and dairy heifers
  A cow or heifer may be noncyclic due to the presence of a luteal cyst (a single, anovulatory follicle with a thickened wall which is accompanied by no external signs and by no changes in palpable consistency of the uterus). Treatment with Estrumate can restore normal ovarian activity by causing regression of the luteal cyst.
5. For abortion of beef cows, lactating dairy cows, and replacement beef and dairy heifers
  Unwanted pregnancies can be safely and efficiently terminated from 1 week after mating until about 5 months of gestation. The induced abortion is normally uncomplicated and the fetus and placenta are usually expelled about 4 to 5 days after the injection with the reproductive tract returning to normal soon after the abortion. The ability of Estrumate to induce abortion decreases beyond the fifth month of gestation while the risk of dystocia and its consequences increases. Estrumate has not been sufficiently tested under feedlot conditions; therefore, recommendations cannot be made for its use in heifers placed in feedlots.
6. For estrus synchronization in beef cows, lactating dairy cows, and replacement beef and dairy heifers
  The luteolytic action of Estrumate can be utilized to schedule estrus and ovulation for an individual cycling animal or a group of animals. This allows control of the time at which cycling cows or heifers can be bred. Estrumate can be used in a breeding program with the following methods:
  - Single Estrumate injection: Only animals with a mature corpus luteum should be treated to obtain maximum response to the single injection. However, not all cycling cattle should be treated since a mature corpus luteum is present for only 11 to 12 days of the 21-day cycle. Prior to treatment, cattle should be examined rectally and found to be anatomically normal, be non-pregnant, and have a mature corpus luteum. If these criteria are met, estrus is expected to occur 2 to 5 days following injection, at which time animals may be inseminated. Treated cattle should be inseminated at the usual time following detection of estrus. If estrous detection is not desirable or possible, treated animals may be inseminated either once at about 72 hours or twice at about 72 and 96 hours post-injection. With a single injection program, it may be desirable to assess the cyclicity status of the herd before Estrumate treatment. This can be accomplished by heat detecting and breeding at the usual time following detection of estrus for a 6-day period, all prior to injection. If by the sixth day the cyclicity status appears normal (approximately 25%-30% detected in estrus), all cattle not already inseminated should be palpated for normality, non-pregnancy, and cyclicity, then injected with Estrumate. Breeding should then be continued at the usual time following signs of estrus on the seventh and eighth days. On the ninth and tenth days, breeding may continue at the usual time following detection of estrus, or all cattle not already inseminated may be bred either once on the ninth day (at about 72 hours post-injection) or on both the ninth and tenth days (at about 72 and 96 hours post-injection).
  - Double Estrumate injections: prior to treatment, cattle should be examined rectally and found to be anatomically normal, nonpregnant, and cycling (the presence of a mature corpus luteum is not necessary when the first injection of a double injection regimen is given). A second injection should be given 11 days after the first injection. In normal, cycling cattle, estrus is expected 2 to 5 days following the second injection. Treated cattle should be inseminated at the usual time following detection of estrus. If estrous detection is not desirable or possible, treated animals may be inseminated either once at about 72 hours or twice at about 72 and 96 hours following the second Estrumate injection. Many animals will come into estrus following the first injection; these animals can be inseminated at the usual time following detected estrus. Animals not inseminated should receive a second injection 11 days after the first injection. Animals receiving both injections may be inseminated at the usual time following detection of estrus or may be inseminated either once at about 72 hours or twice at about 72 and 96 hours post second injection.
  Any breeding program recommended should be completed by either:
  - observing animals (especially during the third week after injection) and inseminating or hand mating any animals returning to estrus, or
  - turning in clean-up bull(s) 5 to 7 days after the last injection of Estrumate to cover any animals returning to estrus.
  Management considerations for use of Estrumate for estrus synchronization:
  A variety of programs can be designed to best meet the needs of individual management systems. A breeding program should be selected which is appropriate for the existing circumstances and management practices. Before a breeding program is planned, the producer's objectives must be examined and the producer must be made aware of the projected results and limitations. The producer and the consulting veterinarian should review the operation's breeding history, herd health, and nutritional status and agree that a breeding program is practical in the producer's specific situation. For any successful breeding program:
  - cows and heifers must be normal, non-pregnant, and cycling (rectal palpation should be performed);
  - cows and heifers must be in sound breeding condition and on an adequate or increasing plane of nutrition;
  - proper program planning and record keeping are essential;
  - if artificial insemination is used, it must be performed by competent inseminators using high-quality semen.
    It is important to understand that Estrumate is effective only in animals with a mature corpus luteum (ovulation must have occurred at least 5 days prior to treatment). This must be considered when breeding is intended following a single Estrumate injection.
  There is no difference in the fertility achieved following the single or double dosage regimen when breeding occurs at induced estrus, or at 72 and 96 hours post-treatment. Conception rates may be lower than expected in those fixed time breeding programs employing Estrumate alone which omit the second insemination (ie, the insemination at or near 96 hours). This is especially true if a fixed time insemination is used following a single Estrumate injection.
7. For use with Fertagyl® (gonadorelin) to synchronize estrous cycles to allow for fixed time artificial insemination (FTAI) in lactating dairy cows
  Use in reproductive synchrony programs similar to the following:
  - Administer the first Fertagyl® injection (2 mL; 86 mcg gonadorelin, as gonadorelin acetate) by intramuscular injection on Day 0.
  - Administer 2 mL of Estrumate by intramuscular injection 6 to 8 days after the first Fertagyl® injection.
  - Administer the second Fertagyl® injection (2mL; 86 mcg gonadorelin, as gonadorelin acetate) 30 to 72 hours after the Estrumate injection.
  - Perform FTAI 8 to 24 hours after the second Fertagyl® injection, or inseminate cows on detected estrus using standard herd practices.

CONTRAINDICATIONS:

Do not use this drug product in pregnant cattle, unless abortion is desired.

WARNINGS AND PRECAUTIONS:

WITHDRAWAL PERIODS AND RESIDUE WARNINGS:

No milk discard or pre-slaughter drug withdrawal period is required when used according to labeling. Use of this product in excess of the approved dose may result in drug residues.

SAFE HANDLING WARNING

USER SAFETY WARNINGS: Not for use in humans. Keep this and all drugs out of the reach of children.

Women of childbearing age, asthmatics, and persons with bronchial and other respiratory problems should exercise extreme caution when handling this product.

Estrumate is readily absorbed through the skin and can cause abortion and/or bronchospasms. Direct contact with the skin should therefore be avoided. Accidental spillage on the skin should be washed off immediately with soap and water.

To obtain a copy of the Safety Data Sheet (SDS) or for technical assistance, contact Merck Animal Health at 1-800-211-3573 or http://www.merck.com

ANIMAL SAFETY WARNINGS:

As with all parenteral products, careful aseptic techniques should be employed to decrease the possibility of post-injection bacterial infection. Severe localized clostridial infections associated with injection of Estrumate have been reported. In rare instances, such infections have resulted in death. Aggressive antibiotic therapy should be employed at the first sign of infection at the injection site, whether localized or diffuse.

At 50 and 100 times the recommended dose, mild side effects may be detected in some cattle. These include increased uneasiness, slight frothing, and milk let-down.

CONTACT INFORMATION:

To report suspected adverse drug experiences, call Merck Animal Health at 1-800-211-3573. For additional information about adverse drug experience reporting for animal drugs, contact FDA at 1-888-FDA-VETS or at http://www.fda.gov/reportanimalae

HOW SUPPLIED:

20 mL and 100 mL multidose vials

STORAGE, HANDLING, AND DISPOSAL:

1. Protect from light.
2. Store in carton.
3. Store at 2-30°C (36-86°F).

See FDA's website http://www.fda.gov/safesharpsdisposal for information on safe disposal of needles and other sharps.

Approved by FDA under NADA # 113-645
Copyright © 2017-2022 Merck & Co., Inc., Rahway, NJ, USA and its affiliates. All rights
reserved. Formulated in Germany

Rev. 06/2022

397732 R1

PRINCIPAL DISPLAY PANEL - 20 mL Vial Carton

NDC 0061-5995-01

10 Doses
20 mL

Estrumate®
(cloprostenol injection)

250 mcg cloprostenol/mL
(equivalent to 263 mcg
cloprostenol sodium/mL)

A sterile solution of a
prostaglandin F2α analogue
for intramuscular injection
in beef cows, lactating dairy
cows, and replacement beef
and dairy heifers.

CAUTION: Federal (USA) law
restricts this drug to use by or
on the order of a licensed
veterinarian.

MERCK
Animal Health